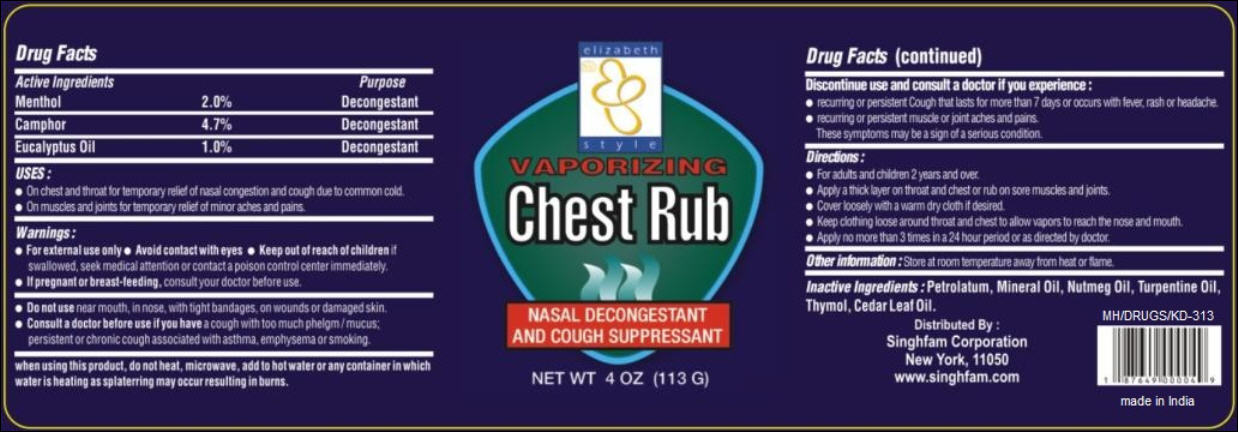 DRUG LABEL: Vaporizing Chest Rub
NDC: 52920-124 | Form: GEL
Manufacturer: Singhfam Corporation
Category: otc | Type: HUMAN OTC DRUG LABEL
Date: 20120124

ACTIVE INGREDIENTS: CAMPHOR (SYNTHETIC) 4.7 g/113 g; MENTHOL 1.1 g/113 g; EUCALYPTUS OIL 1.1 g/113 g
INACTIVE INGREDIENTS: PETROLATUM; MINERAL OIL; NUTMEG OIL; TURPENTINE OIL; THYMOL; CEDAR LEAF OIL

Vaporizing Chest Rub

Active Ingredients

Menthol 2.0%

Camphor 4.7%

Eucalyptus Oil 1.0%

Purpose

Decongestant

USES:

- On chest and throat for temporary relief of nasal congestion and cough due to common cold.
- On muscles and joints for temporary relief of minor aches and pains.

Warnings:

- For external use only
- Avoid contact with eyes

Keep out of reach of children

if swallowed, seek medical attention or contact a poison control center immediately.

If pregnant or breast-feeding,

consult your doctor before use.

Do not use

near mouth, in nose, with tight bandages, on wounds or damaged skin.

Consult a doctor before use

if you have a cough with too much phlegm/mucus; persistent or chronic cough associated with asthma, emphysema or smoking.

when using this product,

do not heat, microwave, add to hot water or any container in which water is heating as splattering may occur resulting in burns.

Discontinue use and consult a doctor

if you experience:

- recurring or persistent Cough that lasts for more than 7 days or occurs with fever, rash or headache.
- recurring or persistent muscle or joint aches and pains.

These symptoms may be a sign of a serious condition.

Directions:

- For adults and children 2 years of age and over.
- Apply a thick layer on throat and chest or rub on sore muscles and joints.
- Cover loosely with a warm dry cloth if desired.
- Keep clothing loose around throat and chest to allow vapors to reach the nose and mouth.
- Apply no more than 3 times in a 24 hour period or as directed by doctor.

Other information:

Store at room temperature away from heat or flame.

Inactive Ingredients:

Petrolatum, Mineral Oil, Nutmeg Oil, Turpentine Oil, Thymol, Cedar Leaf Oil.

PACKAGE LABEL

PRINCIPAL DISPLAY PANEL
elizabeth style
Vaporizing Chest Rub
Nasal Decongestant and Cough Suppressant
NET WT 4 OZ (113 G)